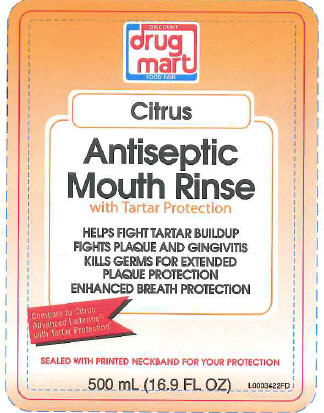 DRUG LABEL: Advanced Antiseptic Citrus
NDC: 53943-210 | Form: MOUTHWASH
Manufacturer: Drug Mart
Category: otc | Type: HUMAN OTC DRUG LABEL
Date: 20250220

ACTIVE INGREDIENTS: EUCALYPTOL 0.92 mg/1 mL; MENTHOL 0.42 mg/1 mL; METHYL SALICYLATE 0.6 mg/1 mL; THYMOL 0.64 mg/1 mL
INACTIVE INGREDIENTS: WATER; ALCOHOL; SORBITOL; POLYOXYL 40 HYDROGENATED CASTOR OIL; POLOXAMER 407; BENZOIC ACID; ZINC CHLORIDE; SUCRALOSE; SODIUM BENZOATE; FD&C YELLOW NO. 6; FD&C RED NO. 40

Discount Drug Mart 210
Citrus mw

Active ingredients

Eucalyptol 0.092%, Menthol 0.042%
Methyl salicylate 0.060%, Thymol 0.064%

Purpose

Antigingivitis, Antiplaque

Use

helps control plaque that leads to gingivitis

Warnings

for this product

Do not use

if you have painful or swollen gums, puss from the gum line, loose teeth or increased spacing between the teeth. See your
dentist immediately. These may be signs of periodontitis, a serious form of gum disease

Stop use and ask a dentist if

gingivitis, bleeding, or redness persists for more than 2 weeks.

Keep out of reach of children.

If more than used for rinsing is accidentally swallowed, get medical help or contact a Poison Control Center right away.

Directions

adults and children 12 years of age and older - vigorously swish 20 mL (2/3 FL OZ or 4 teaspoonfuls) between teeth for 30 seconds then spit out: do not swallow
children under 12 years of age - consult a dentist or doctor
•this reinse is not intended to replace brushing or flossing

Other information

cold weather may cloud this product. Its antiseptic properties are not affected. Store at room temperature (59⁰- 77⁰ F)

Inactive ingredients

water, alcohol (21.6%), sorbitol solution, flavoring, PEG-40 hydrogenated castor oil, poloxamer 407, benzoic acid, zinc chloride,
sucralose and/or sodium saccharin, sodium benzoate, yellow 6, red 40

Disclaimer

This product is not manufactured or distributed by Johnson + Johnson Healthcare Products, distributor of Listerine
DSP-TN-15000
DSP-MO-34
SDS-TN-15012

ADVERSE REACTION

DISTRIBUTED BY
DRUG MART-FOOD FAIR
MEDINA, OHIO 44256
WWW.DISCOUNT-DRUGMART.COM

PRINCIPAL DISPLAY PANEL

Discount
Drug
Mart
Food Fair
Citrus
Antiseptic
Mouth Rinse
with Tartar Protection
HELPS FIGHT TARTAR BUILDUP
FIGHTS PLAQUE AND GINGIVITIS
KILLS GERMS FOR EXTENDED
PLAQUE PROTECTION
ENHANCED BREATH PROTECTION
Compare To Citrus
Advanced Listerine
with Tartar Protection
SEALED WITH PRINTED NECKBAND FOR YOUR PROTECTION
500 mL (16.9 FL OZ)